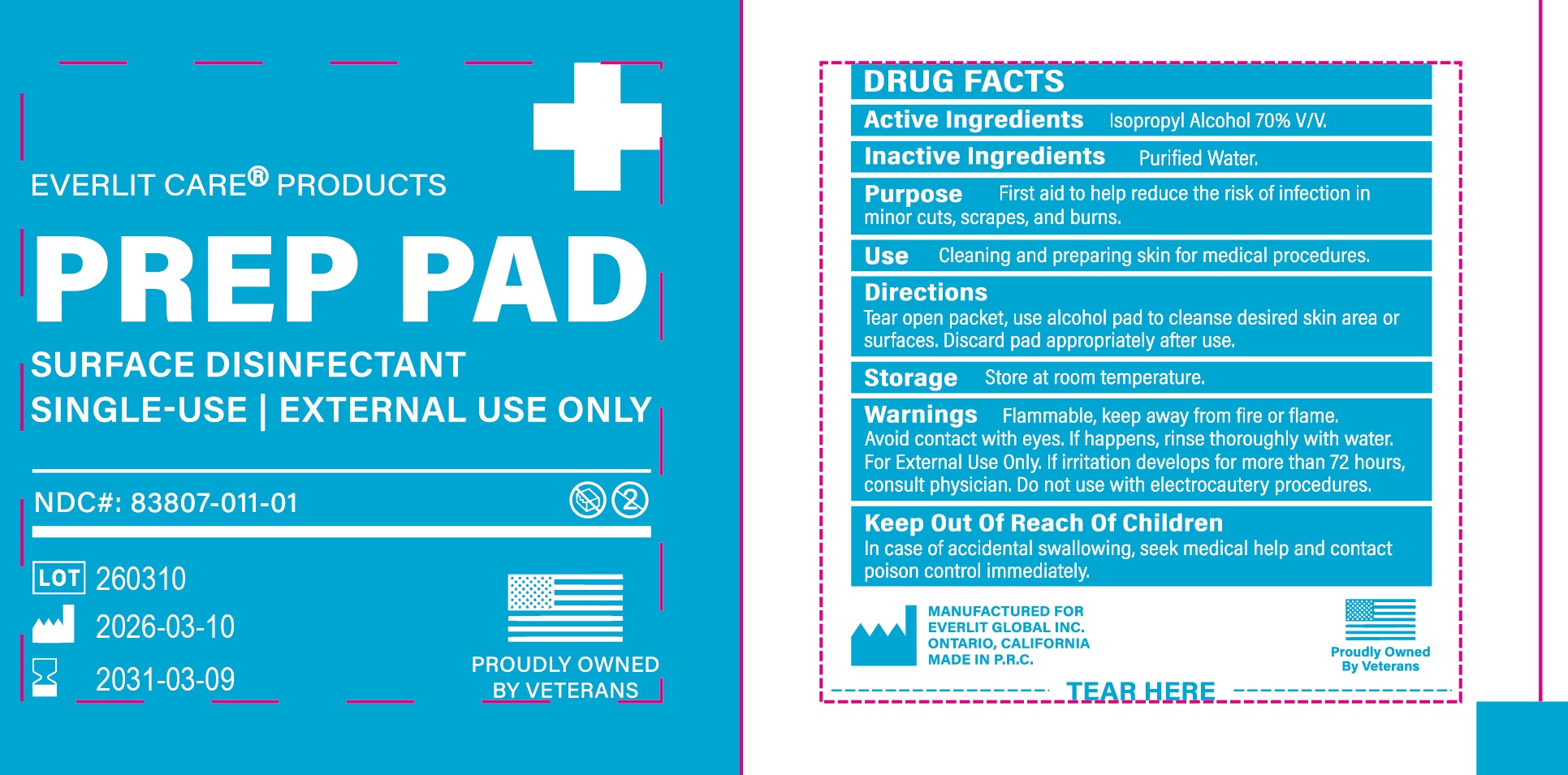 DRUG LABEL: EVERLIT CARE PRODUCTS PREP PAD
NDC: 83807-011 | Form: CLOTH
Manufacturer: EVERLIT GLOBAL INC.
Category: otc | Type: HUMAN OTC DRUG LABEL
Date: 20260209

ACTIVE INGREDIENTS: ISOPROPYL ALCOHOL 0.34 g/1 1
INACTIVE INGREDIENTS: WATER

83807-011 EVERLIT CARE PRODUCTS Prep PAD

Active Ingredient

Isopropyl Alcohol, 70% v/v

Purpose

First aid to help reduce the risk of infection in minor cuts, srapes, and burns

Uses

Cleaning and preparing skin for medical procedures

Warnings

Flammable. Keep away from fire or flame.

Avoid contact with the eyes. If happens, rinse thoroughly with water

For external ue only

Do Not Use

With electrocautery prodedures

STOP USE

If irritation develops for more than 72 hours, consult a physician

Keep out of reach of children

In case of accidental swallowing, seek medical help or contact a Poison Control Center immediately

Directions

Tear open packet, use alcohol pad to cleanse desired skin area or surfaces. Discard pad appropriately after use

Other Information

Store at room temperature

Inactive Ingredients

Purified Water